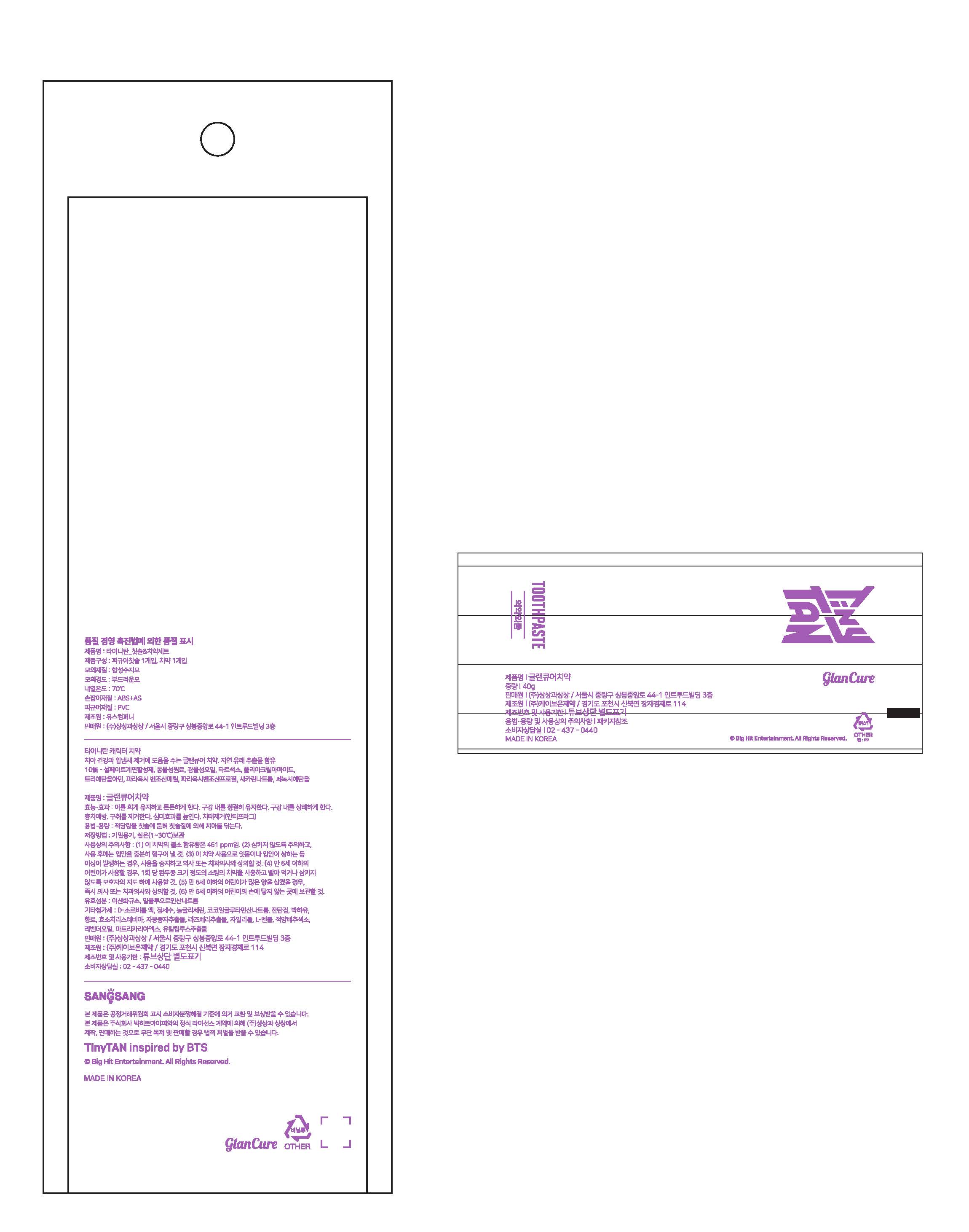 DRUG LABEL: Glancure Tooth
NDC: 74724-0015 | Form: PASTE
Manufacturer: K.Boeun Pharmaceutical Co.,Ltd.
Category: otc | Type: HUMAN OTC DRUG LABEL
Date: 20200915

ACTIVE INGREDIENTS: SODIUM MONOFLUOROPHOSPHATE 0.35 g/100 g
INACTIVE INGREDIENTS: XANTHAN GUM; XYLITOL; SILICON DIOXIDE

Drug Facts

ACTIVE INGREDIENT

Sodium monofluorophosphate

INACTIVE INGREDIENT

Silicon Dioxide, D-Sorbitol Solution, Water, Concentrated Glycerin, Sodium Cocoyl Glutamate, Xanthan ?Gum, Peppermint Oil, Flavor, Enzymatically Modified Stevia, Citrus Paradisi (Grapefruit) Seed Extract, Raspberry Extract, Xylitol, L-Menthol, Red Cabbage Color, Lavender Oil, Chamomile Extract, Eucalyptus Extract

PURPOSE

for dental care

KEEP OUT OF REACH OF THE CHILDREN

INDICATIONS AND USAGE

Adults and children 2 years of age and older: Brush teeth thoroughly, preferably after each meal or at least twice a day, or as directed by a dentist or doctor.

Children 2 to 6 years of age: Instruct children under 6 years of age in good brushing and rinsing habits (to minimize swallowing). Supervise children as necessary until capable of using without supervision.

Children under 2 years of age: Consult a dentist or doctor.

WARNINGS

Do not swallow.

Keep out of reach of children. If swallowed, get medical help or contact a Poison Control Center right away.

DOSAGE AND ADMINISTRATION

For dental use only